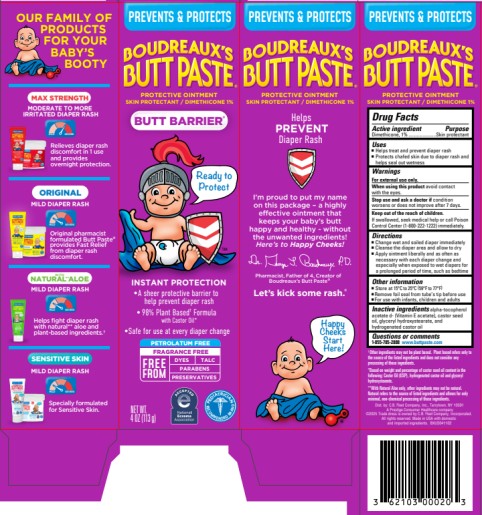 DRUG LABEL: Boudreauxs Butt Barrier
NDC: 0132-0326 | Form: OINTMENT
Manufacturer: C.B. Fleet Company, Inc.
Category: otc | Type: HUMAN OTC DRUG LABEL
Date: 20251027

ACTIVE INGREDIENTS: DIMETHICONE 1 g/113 g
INACTIVE INGREDIENTS: .ALPHA.-TOCOPHEROL ACETATE; CASTOR OIL; GLYCERYL HYDROXYSTEARATE; HYDROGENATED CASTOR OIL

Boudreauxs Butt Barrier ointment_dimethicone_0132-0326

BOUDREAUXS BUTT BARRIER- dimethicone ointment
C.B. Fleet Company, Inc.

----------

Boudreauxs Butt Barrier ointment_dimethicone_0132-0326

Drug Facts

Active ingredient

Dimethicone, 1%

Purpose

Skin protectant

Uses

- Helps treat and prevent diaper rash
- Protects chafed skin due to diaper rash and helps seal out wetness

Warnings

For external use only

When using this product

avoid contact with the eyes

Stop use and ask a doctor if

condition worsens or does not improve after 7 days

Keep out of reach of children

If swallowed, seek medical help or call poison control center (1-800-222-1222) immediately.

Directions

- Change wet and soiled diaper immediately
- Cleanse the diaper area and allow to dry
- Apply ointment liberally and as often as necessary with each diaper change and especially when exposed to wet diapers for a prolonged period of time, such as bedtime

Other information

- Store at 15-25° C (59-77° F)
- Remove foil seal from tube’s tip before use
- For use with infants, children and adults

Inactive ingredients

Alpha-tocopherol acetate d- (Vitamin E acetate), castor seed oil, glyceryl hydroxystearate, and hydrogenated castor oil

Questions

1-855-785-2888

www. buttpaste.com

Principal Display Panel

Boudreaux’s Butt Paste®
Butt Barrier
Protective Ointment
Skin protectant / Dimethicone 1%

NET WT. 4 oz (113 g)